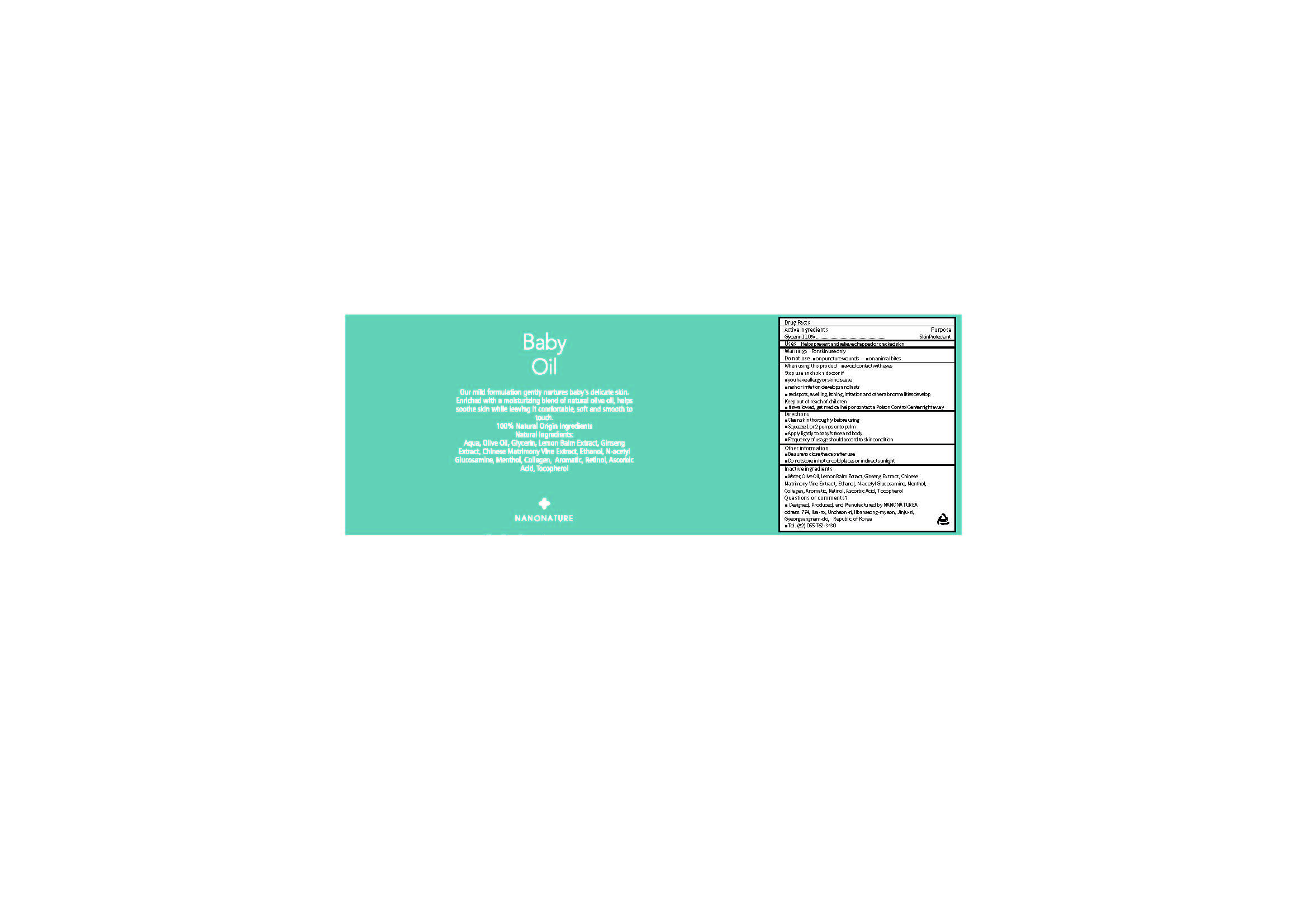 DRUG LABEL: Baby Oil
NDC: 71538-006 | Form: SOLUTION
Manufacturer: NANONATURE
Category: otc | Type: HUMAN OTC DRUG LABEL
Date: 20170717

ACTIVE INGREDIENTS: Glycerin 11 g/100 mL
INACTIVE INGREDIENTS: Water; Olive Oil; Retinol; Tocopherol; Ascorbic Acid

ACTIVE INGREDIENT

Glycerin (11.0%) - Skin Protectant

INACTIVE INGREDIENT

Water, Olive Oil, Lemon Balm Extract, Ginseng Extract, Chinese Matrimony Vine Extract, Ethanol, N-acetyl Glucosamine, Menthol, Collagen, Aromatic, Retinol, Ascorbic Acid, Tocopherol

PURPOSE

Skin Protectant

WARNINGS

When using this product
 avoid contact with eyes
Stop use and ask a doctor if
 you have allergy or skin disease
 rash or irritation develops and lasts
 red spots, swelling, itching, irritation and other abnormalities develops

KEEP OUT OF REACH OF CHILDREN

 if swallowed, get medical help or contact a Poison Control Center right away

INDICATIONS & USAGE

 Clean skin thoroughly before using
 Squeeze 1 or 2 pumps onto palm
 Apply lightly to baby’s face and body
 Frequency of usage should accord to skin condition

DOSAGE & ADMINISTRATION

 Clean skin thoroughly before using
 Squeeze 1 or 2 pumps onto palm
 Apply lightly to baby’s face and body
 Frequency of usage should accord to skin condition